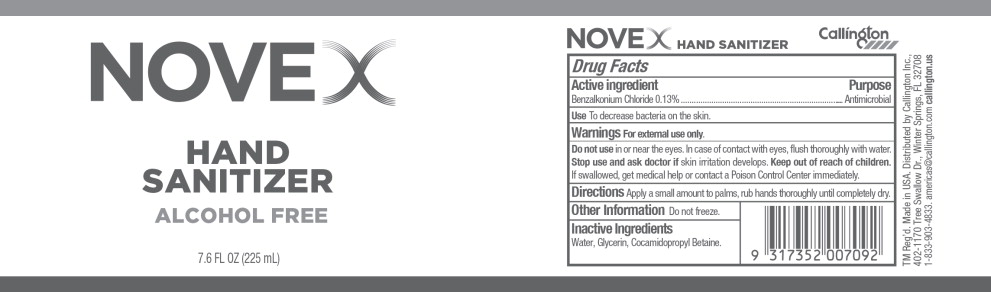 DRUG LABEL: Novex Hand Sanitizer
NDC: 66902-037 | Form: LIQUID
Manufacturer: Natural Essentials, Inc.
Category: otc | Type: HUMAN OTC DRUG LABEL
Date: 20240320

ACTIVE INGREDIENTS: BENZALKONIUM CHLORIDE 1.3 mg/1 mL
INACTIVE INGREDIENTS: WATER; GLYCERIN; COCAMIDOPROPYL BETAINE

Drug Facts

Active ingredient

Benzalkonium Chloride 0.13%

Purpose

Antimicrobial

Use

To decrease bacteria on the skin.

Warnings

For external use only.

Do not use in or near the eyes. In case of contact with eyes, flush thoroughly with water.

Stop use and ask doctor if skin irritation develops.

Keep out of reach of children.

If swallowed, get medical help or contact a Poison Control Center immediately.

Directions

Apply a small amount to palms, rub hands thoroughly until completely dry.

Other Information

Do not freeze.

Inactive Ingredients

Water, Glycerin, Cocamidopropyl Betaine.

Principal Display Panel – 225 mL Bottle Label

NOVEX

HAND
SANITIZER

ALCOHOL FREE

7.6 FL OZ (225 mL)